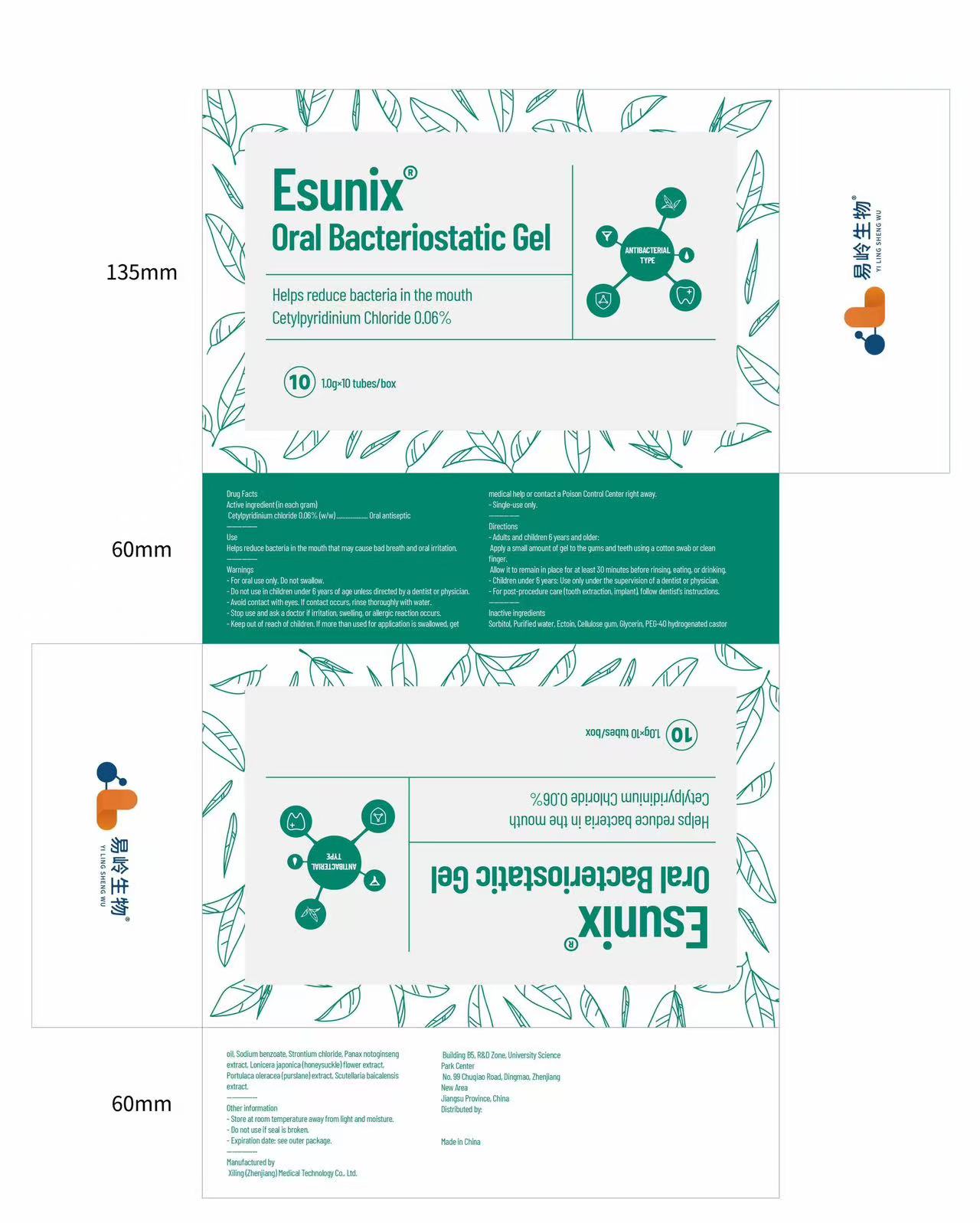 DRUG LABEL: Esunix Oral Bacteriostatic Gel
NDC: 87118-006 | Form: GEL, DENTIFRICE
Manufacturer: Xiling (Zhenjiang) Medical Technology Co., Ltd.
Category: otc | Type: HUMAN OTC DRUG LABEL
Date: 20251212

ACTIVE INGREDIENTS: CETYLPYRIDINIUM CHLORIDE 0.06 g/100 g
INACTIVE INGREDIENTS: PANAX NOTOGINSENG WHOLE; ECTOIN; CELLULOSE GUM; PORTULACA OLERACEA WHOLE; WATER; SCUTELLARIA BAICALENSIS WHOLE; PEG-40 HYDROGENATED CASTOR OIL; SODIUM BENZOATE; SORBITOL; STRONTIUM CHLORIDE; LONICERA JAPONICA FLOWER

ACTIVE INGREDIENT

Cetylpyridinium chloride 0.06% (w/w)

PURPOSE

Oral antiseptic

DOSAGE AND ADMINISTRATION

Helps reduce bacteria in the mouth that may cause bad breath and oral irritation.

WARNINGS

For oral use only. Do not swallow.

Do not use in children under 6 years of age unless directed by a dentist or physician.

Avoid contact with eyes. If contact occurs, rinse thoroughly with water.

Stop use and ask a doctor if irritation, swelling, or allergic reaction occurs.

Keep out of reach of children. If more than used for application is swallowed, get medical help or contact a Poison Control Center right away.

Single-use only.

INDICATIONS AND USAGE

Adults and children 6 years and older:
Apply a small amount of gel to the gums and teeth using a cotton swab or clean finger.
Allow it to remain in place for at least 30 minutes before rinsing, eating, or drinking.

Children under 6 years: Use only under the supervision of a dentist or physician.

For post-procedure care (tooth extraction, implant), follow dentist's instructions.

INACTIVE INGREDIENT

Sorbitol, Purified water, Ectoin, Cellulose gum, Glycerin, PEG-40 hydrogenated castor oil, Sodium benzoate, Strontium chloride, Panax notoginseng extract, Lonicera japonica (honeysuckle) flower extract, Portulaca oleracea (purslane) extract, Scutellaria baicalensis extract.

OTHER SAFETY INFORMATION

Store at room temperature away from light and moisture.

Do not use if seal is broken.

Expiration date: See outer package.

keep out of reach of children